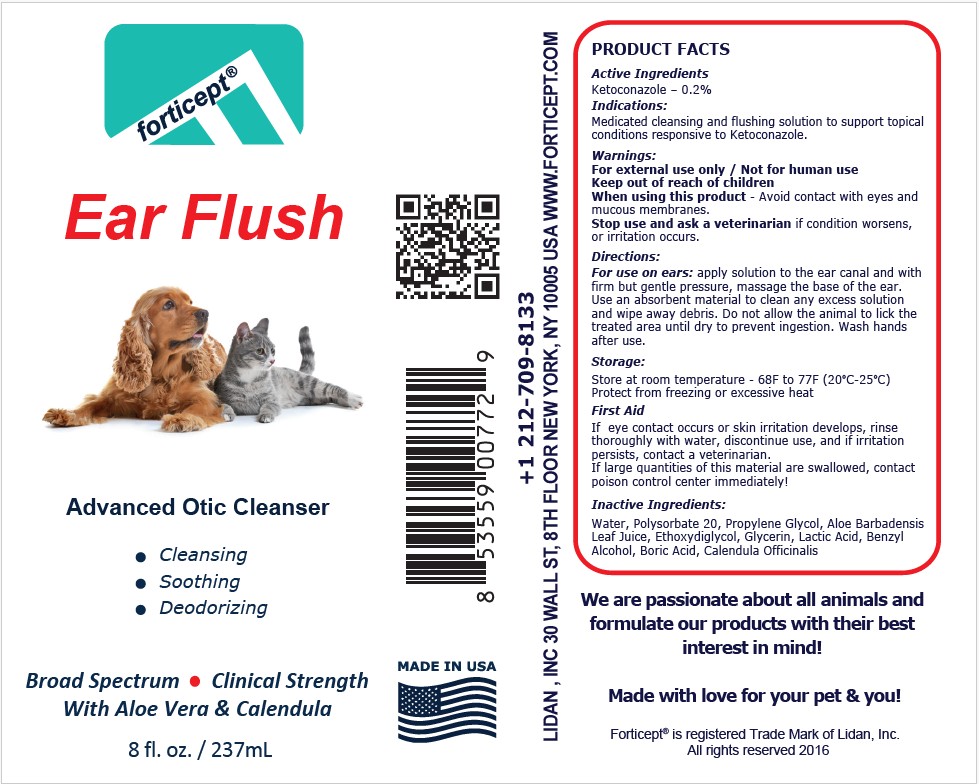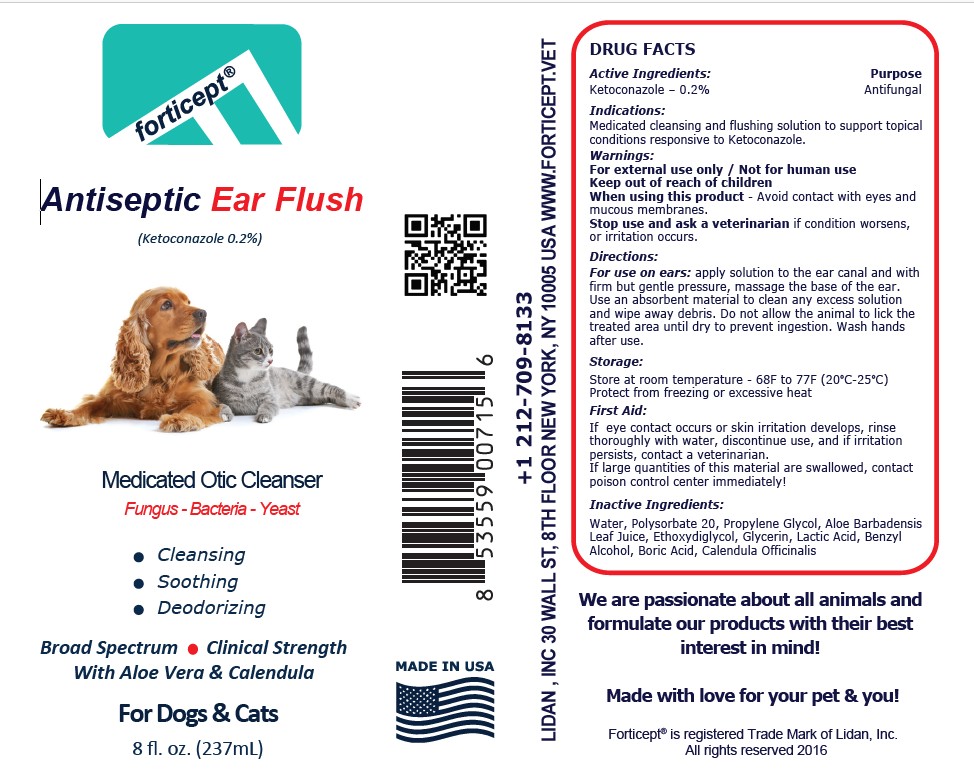 DRUG LABEL: Forticept Antiseptic Ear Flush
NDC: 72127-0904 | Form: LIQUID
Manufacturer: Lidan, Inc.
Category: animal | Type: OTC ANIMAL DRUG LABEL
Date: 20251114

ACTIVE INGREDIENTS: KETOCONAZOLE 2 g/1000 g
INACTIVE INGREDIENTS: WATER; POLYSORBATE 20; PROPYLENE GLYCOL; ALOE VERA LEAF; DIETHYLENE GLYCOL MONOETHYL ETHER; GLYCERIN; LACTIC ACID; BENZYL ALCOHOL; BORIC ACID; CALENDULA OFFICINALIS FLOWER

Forticept Antiseptic Ear Flush - Medicated Otic Cleanser

Active Ingredient(s):

Ketoconazole.......0.2% (Antifungal)

Indications:

Medicated cleansing and flushing solution to support topical conditions responsive to Ketoconazole.

Warnings:

For external use only / Not for human use
Keep out of reach of children
When using this product - Avoid contact with eyes and mucous membranes.
Stop use and ask a veterinarian if condition worsens, or irritation occurs.

Directions:

For use on ears: apply solution to the ear canal and with firm but gentle pressure, massage the base of the ear.
Use an absorbent material to clean any excess solution and wipe away debris. Do not allow the animal to lick the
treated area until dry to prevent ingestion. Wash hands after use.

Storage:

Store at room temperature - 68F to 77F (20°C-25°C)
Protect from freezing or excessive heat

First Aid:

If eye contact occurs or skin irritation develops, rinse thoroughly with water, discontinue use, and if irritation persists, contact a veterinarian.
If large quantities of this material are swallowed, contact poison control center immediately!

Inactive ingredients:

Water, Polysorbate 20, Propylene Glycol, Aloe Barbadensis Leaf Juice, Ethoxydiglycol, Glycerin, Lactic Acid, Benzyl Alcohol, Boric Acid, Calendula Officinalis